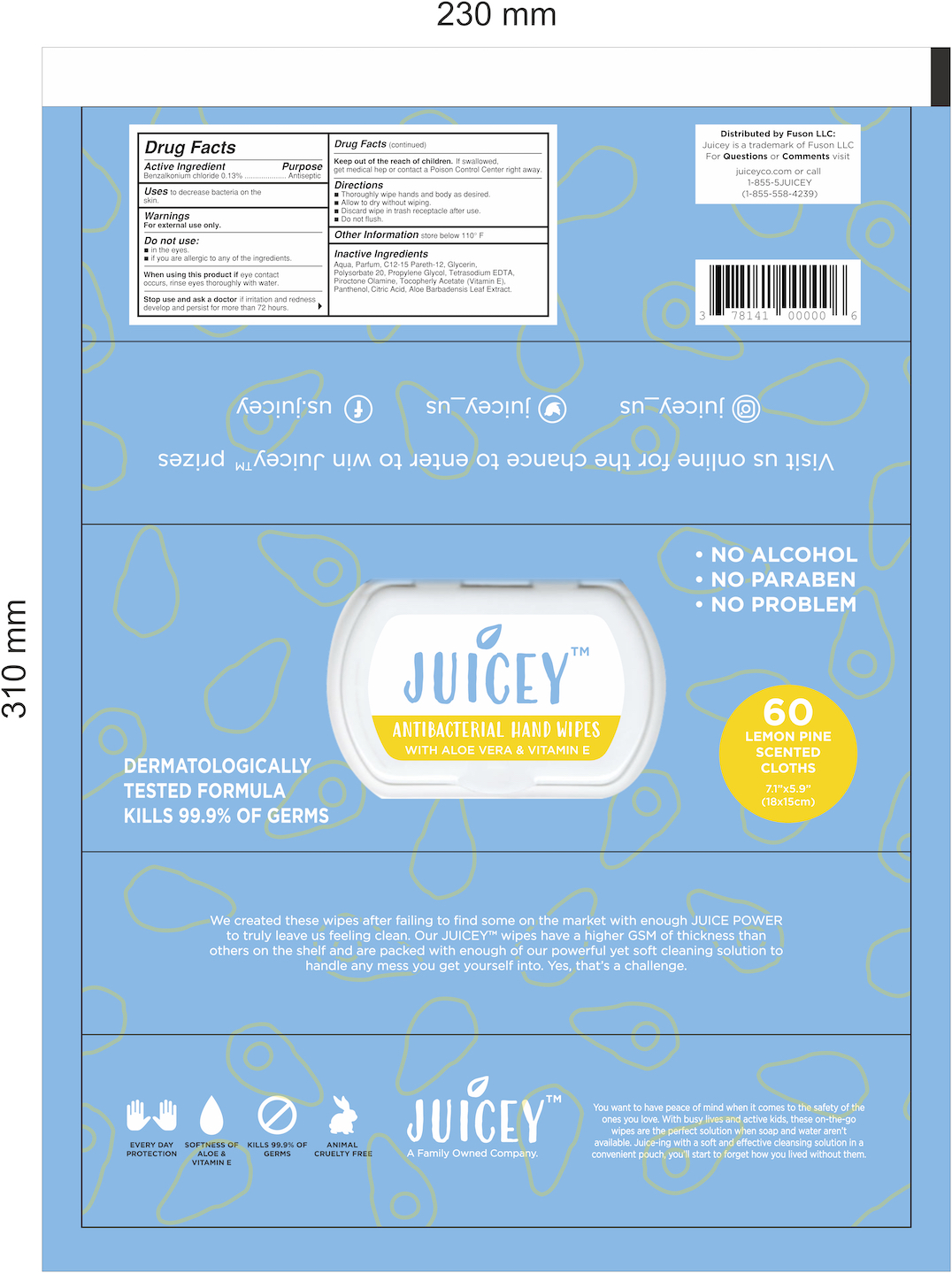 DRUG LABEL: Juicey Antibacterial Wipes
NDC: 78141-901 | Form: CLOTH
Manufacturer: Fuson LLC
Category: otc | Type: HUMAN OTC DRUG LABEL
Date: 20201028

ACTIVE INGREDIENTS: BENZALKONIUM CHLORIDE 0.007 g/5.33 g
INACTIVE INGREDIENTS: EDETATE SODIUM; ALOE VERA LEAF; .ALPHA.-TOCOPHEROL ACETATE; WATER; POLYSORBATE 20; PROPYLENE GLYCOL; GLYCERIN; PANTHENOL; C12-15 PARETH-12; PIROCTONE OLAMINE; CITRIC ACID MONOHYDRATE

Juicey Antibacterial Wipes Pouch

Active Ingredient

Benzalkonium Chloride .13% v/v - Antiseptic

Inactive Ingredients

Aqua, Parfum, C12-15 Pareth-12, Glycerin, Polysorbate 20, Propylene Glycol, Tetrasodium EDTA, Piroctone Olamine, Tocopheryl Acetate (Vitamin E), Panthenol, Citric Acid, Aloebarbadensis Leaf Extract

Purpose

Antiseptic- antibacterial hand towelettes

Use

Wipes used on hands to reduce bacteria on the skin

Warnings

Keep away from flame and direct sunlight. Children should not use this product without adult supervision. For external use only. If ingested, contact a poison control center or seek medical attention. Keep away from eyes.

Do not use if allergic to any of its ingredients. Do not use near eyes. Do not use on children under 2 months of age. Consult a doctor before use if pregnant, breastfeeding, are under the age of 6, or have sensitibe skin.

When Using

If eye contact occurs, remove any contact lenses and flush eyes with water repeatedly. If swallowed, contact a poinson control center immediately or seek medical attention.

KEEP OUT OF REACH OF CHILDREN

Store product out of reach of children. Children under the age of 12 should be supervised during use.

Directions

Open the hard plastic snap cover to reveal the adhesive label that reads, "OPEN". Peel back the adhesive label and remove one wipe at a time. Wipe your hands with the antibacterial wipe until all of the solution is absorbed. Seal the packaging tightly closed when done.

Storage

Store out of reach of children. Store in a cool, dry place. Do not store near food, drinks, or animal feed. Store away from direct sunlight and open flame.

Package Label

60 Count Antibacterial Wipes Pouch NDC: 78141-901